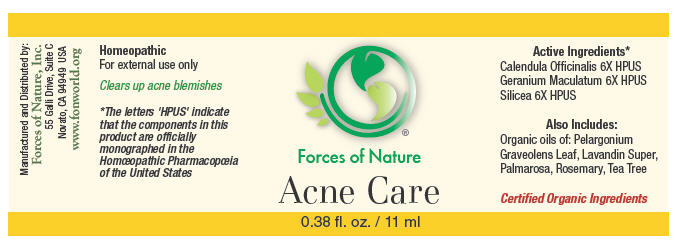 DRUG LABEL: Acne Care
NDC: 51393-6111 | Form: SOLUTION/ DROPS
Manufacturer: Forces of Nature
Category: homeopathic | Type: HUMAN OTC DRUG LABEL
Date: 20100824

ACTIVE INGREDIENTS: CALENDULA OFFICINALIS FLOWERING TOP 6 [hp_X]/1000 mL; GERANIUM MACULATUM ROOT 6 [hp_X]/1000 mL; Silicon Dioxide 6 [hp_X]/1000 mL

Acne Care

Drug Facts

Indications

Clears up acne blemishes; for the relief of skin inflammation, soreness and redness associated with acne.

ACTIVE INGREDIENT

PURPOSE

Homeopathic Active Ingredients [The letters 'HPUS' indicate that the components in this product are officially monographed in the Homœopathic Pharmacopœia of the United States.]
Equal parts of: | Purpose
Calendula Officinalis 6X | promotes healthy skin
Geranium maculatum 6X | helps unhealthy skin, skin ulcers, helps clear acne
Silicea 6X | helps acne, face eruptions

Inactive Ingredients

Pelargonium Graveolens Leaf Oil, Lavandin Oil, Palmarosa Oil, Rosemary Oil, Tea Tree Oil

Directions

Wash face thoroughly with soap and warm water. Moisten cotton ball with warm water. Allow 2-3 drops of product to fall onto moistened cotton ball. Gently rub moistened cotton ball over all areas of acne. Can also be applied directly from the bottle. Repeat process three times per day.

Warnings

Some individuals may be sensitive to essential oils. Begin with a small drop to determine if the product causes any increased redness or irritation and discontinue use if it irritates your skin.

PREGNANCY OR BREAST FEEDING

As with any drug if you are pregnant or breast feeding, seek the advice of a health care professional before using this product.

WHEN USING

For external use only. Do not apply to the eyes or mucous membranes.

KEEP OUT OF REACH OF CHILDREN

Keep all medicines out of the reach of children. In case of accidental ingestion more of than several drops of product, or if any adverse reaction occurs, get medical help or contact a Poison Control Center.

Using other topical acne medications at the same time or immediately following use of this product may increase dryness or irritation of the skin. If this occurs, only one medication should be used unless directed by a doctor.

Manufactured by:
Forces of Nature, Inc.
55 Galli Drive, Suite C
Novato, CA 94949 USA
www.fonworld.org

Product questions?

877-975-3797

NDC#: 51393-1233-1 (11ml) // 51393-1233-2 (33ml)

Principal Display Panel - 11 ml Bottle Label

Forces of Nature

Acne Care

0.38 fl. oz. / 11 ml